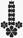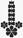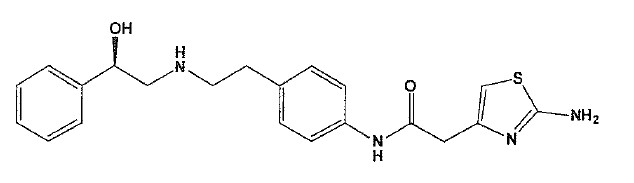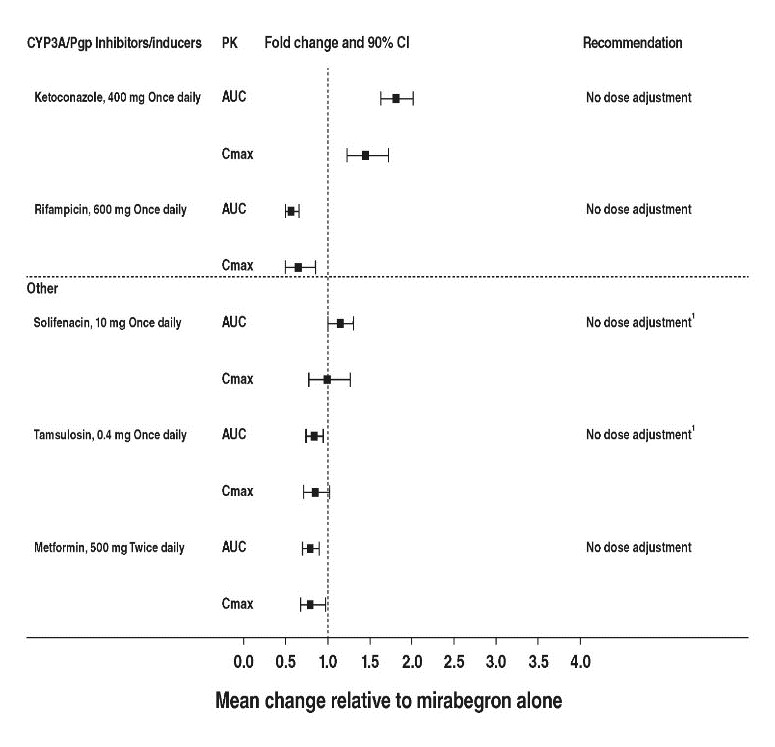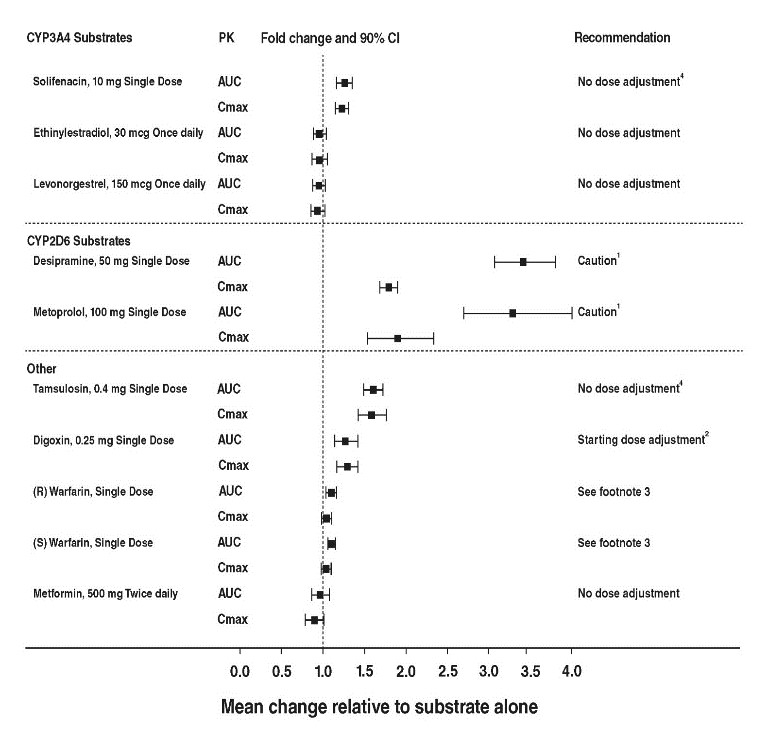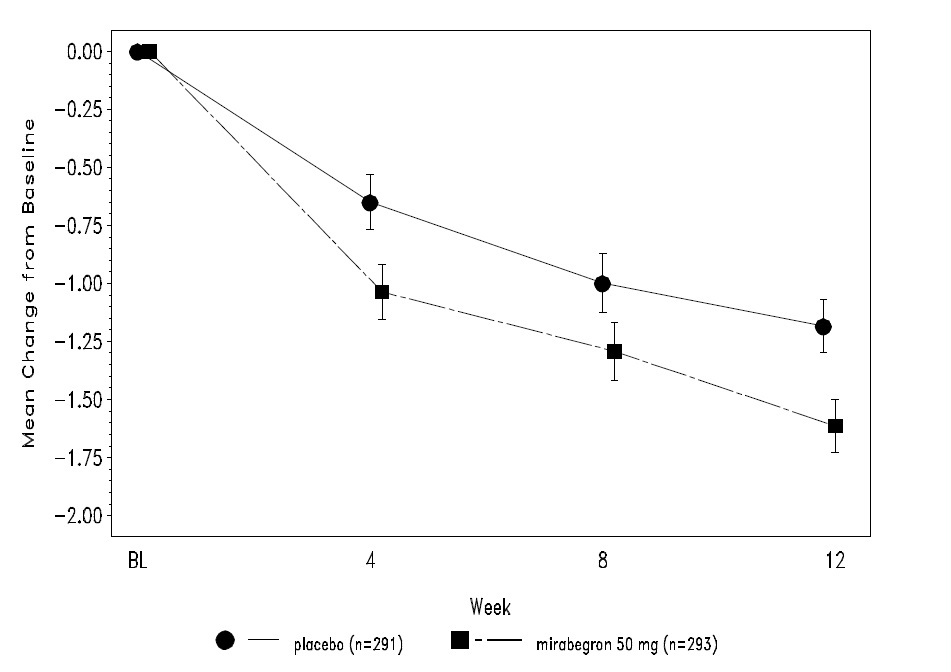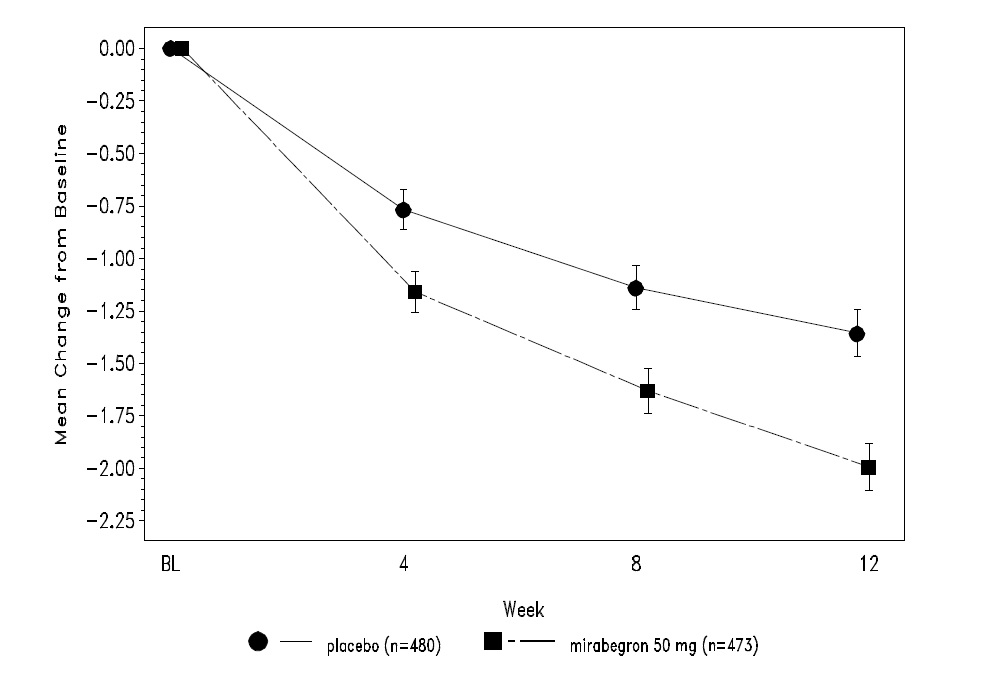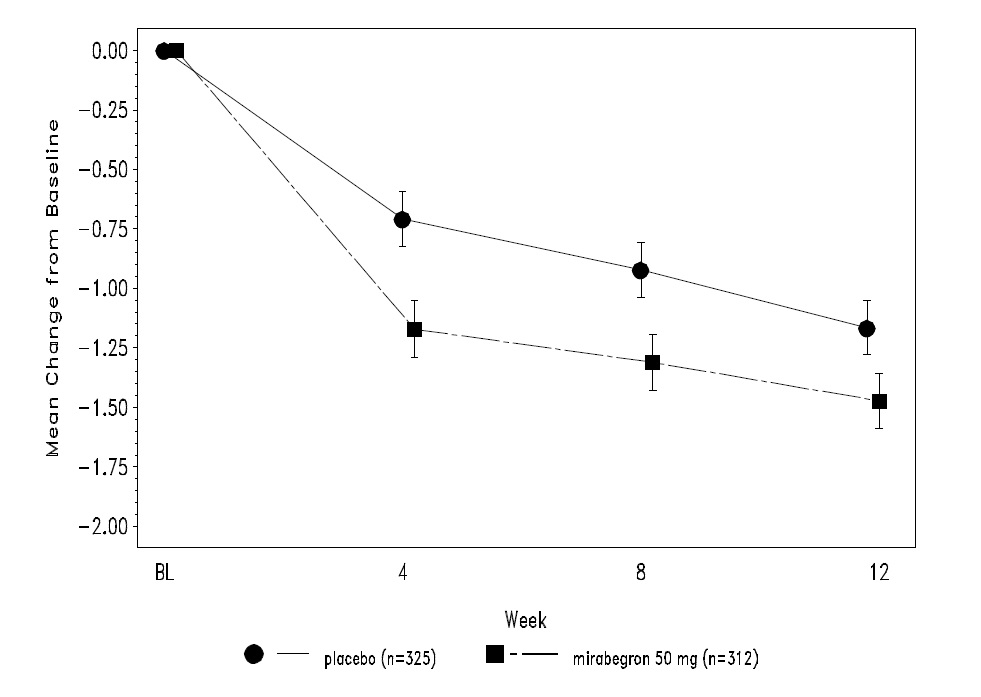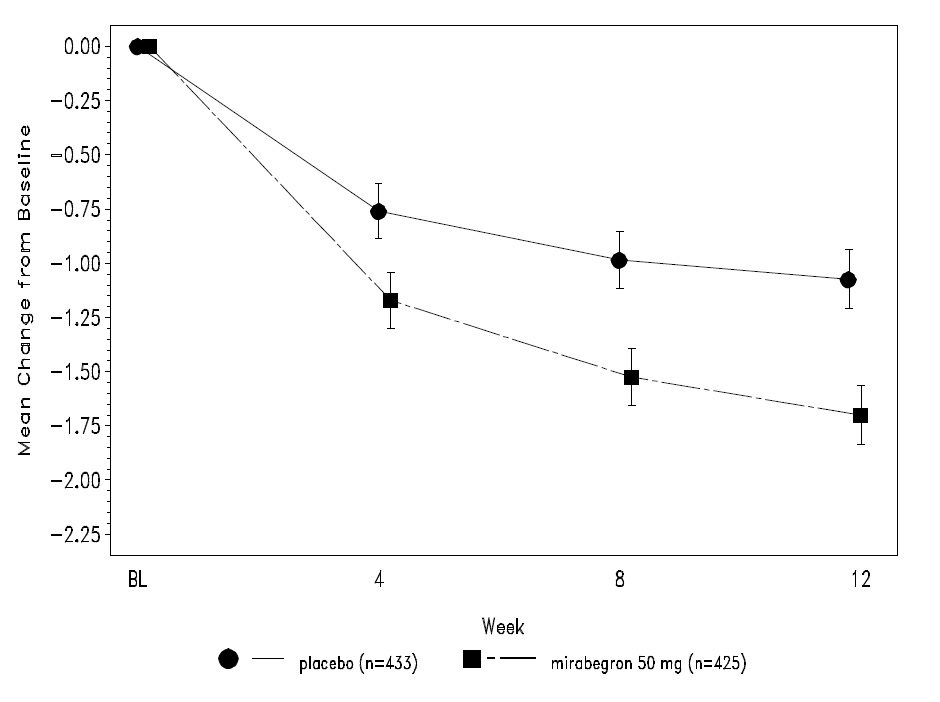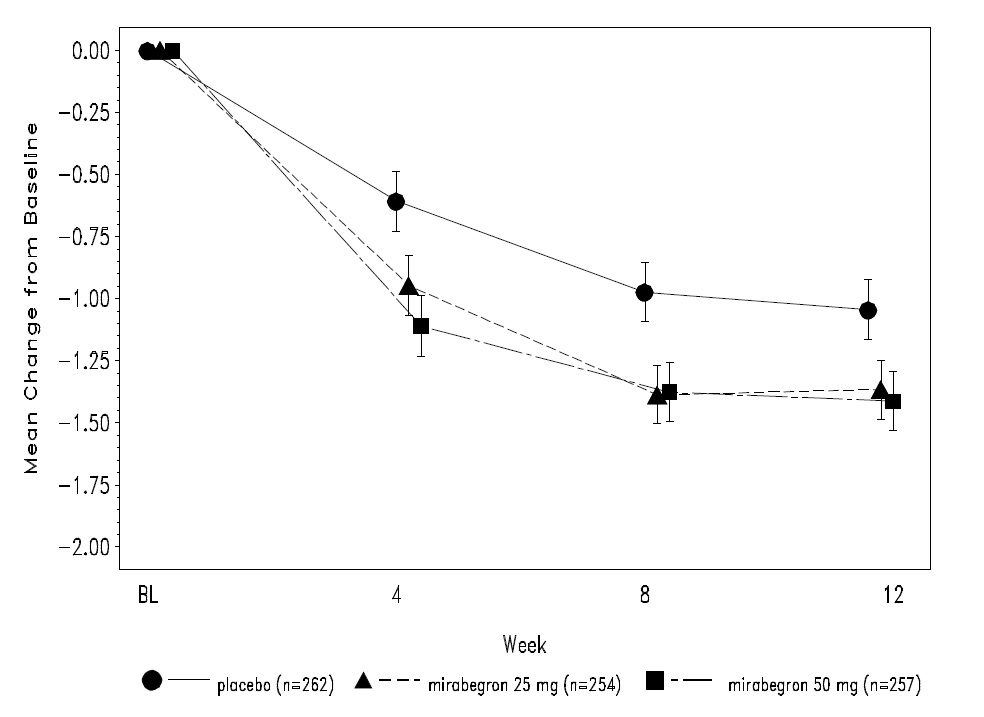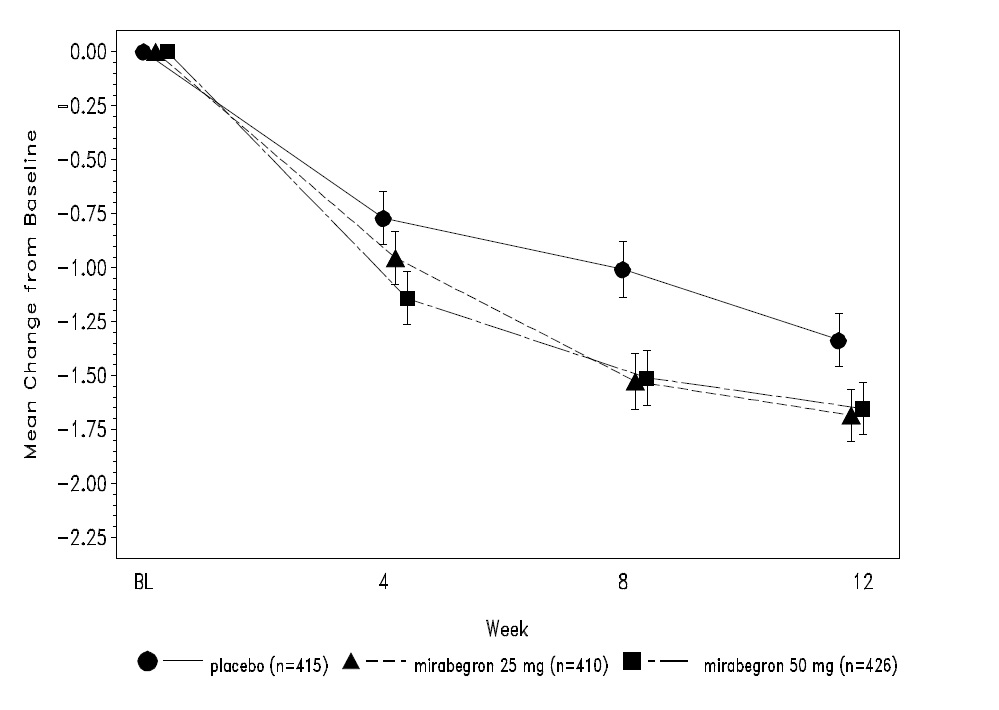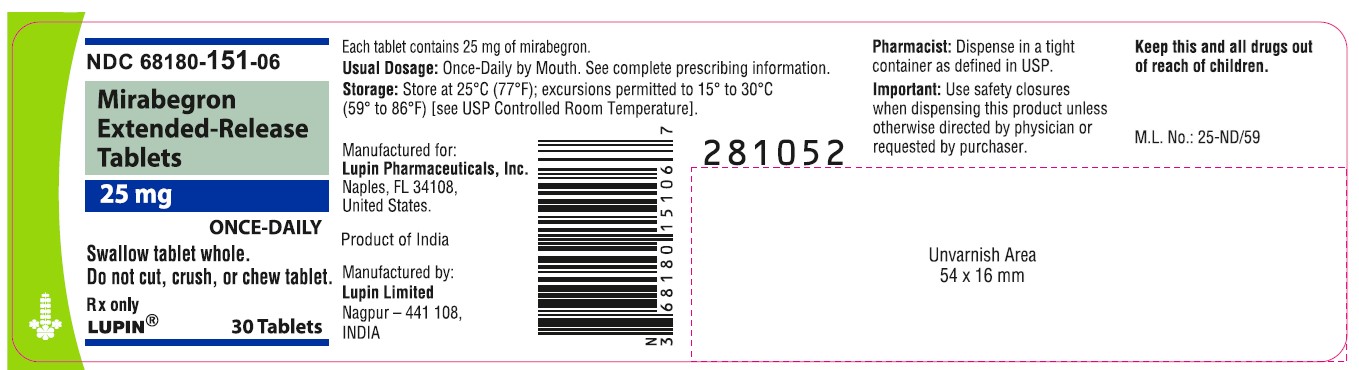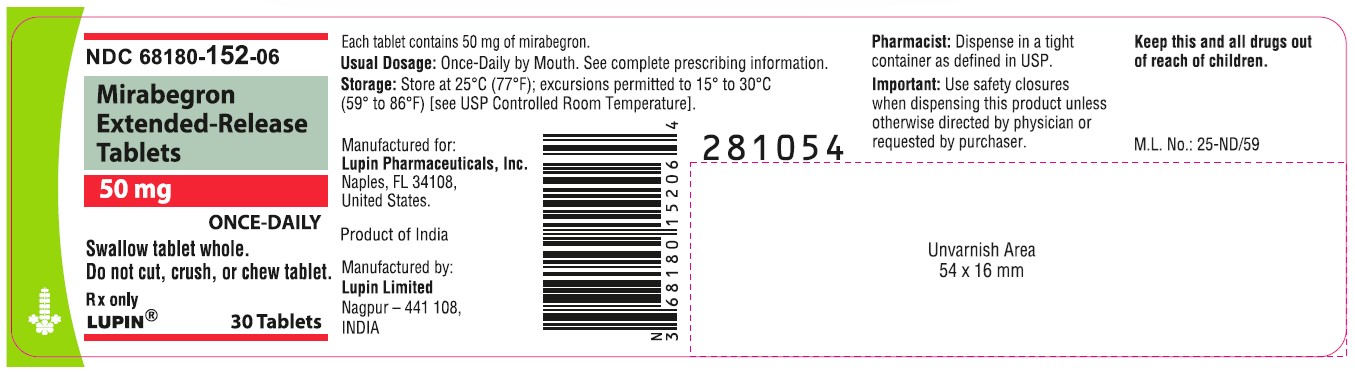 DRUG LABEL: MIRABEGRON
NDC: 68180-151 | Form: TABLET, FILM COATED, EXTENDED RELEASE
Manufacturer: Lupin Pharmaceuticals, Inc.
Category: prescription | Type: HUMAN PRESCRIPTION DRUG LABEL
Date: 20251224

ACTIVE INGREDIENTS: MIRABEGRON 25 mg/1 1
INACTIVE INGREDIENTS: BUTYLATED HYDROXYTOLUENE; HYDROXYPROPYL CELLULOSE (1600000 WAMW); HYPROMELLOSE 2910 (6 MPA.S); MAGNESIUM STEARATE; CELLULOSE, MICROCRYSTALLINE; POLYETHYLENE GLYCOL 6000; POLYETHYLENE OXIDE 1000000; TITANIUM DIOXIDE; TRIACETIN

HIGHLIGHTS OF PRESCRIBING INFORMATION

These highlights do not include all the information needed to use MIRABEGRON EXTENDED-RELEASE TABLETS safely and effectively. See full prescribing information for MIRABEGRON EXTENDED-RELEASE TABLETS.
MIRABEGRON extended-release tablets, for oral use
Initial U.S. Approval: 2012

1 INDICATIONS AND USAGE

Mirabegron extended-release tablets are beta-3 adrenergic agonist indicated for the treatment of:

- Overactive bladder (OAB) in adult patients with symptoms of urge urinary incontinence, urgency, and urinary frequency. (1.1)

2 DOSAGE AND ADMINISTRATION

- Mirabegron extended-release tablets and mirabegron for extended-release oral suspension are two different products and they are not substitutable on a milligram-per-milligram basis. Select the recommended product (mirabegron extended-release tablets or mirabegron for extended-release oral suspension) based on the indication.

OAB in Adults

- The recommended starting dose of mirabegron extended-release tablets is 25 mg orally once daily. (2.2)
- After 4 to 8 weeks, the mirabegron extended-release tablets dose may be increased to 50 mg orally once daily. (2.2)

Adult Patients with Renal or Hepatic Impairment: Refer to the full prescribing information for recommended dosage. (2.4)

Administration

- Mirabegron Extended-Release Tablets:
  - Adult patients: Swallow mirabegron extended-release tablets whole with water. Do not chew, divide, or crush. Take with or without food. (2.7)

3 DOSAGE FORMS AND STRENGTHS

- Extended-release tablets: 25 mg and 50 mg (3)

4 CONTRAINDICATIONS

Hypersensitivity to mirabegron or any inactive ingredients. (4)

5 WARNINGS AND PRECAUTIONS

Increases in Blood Pressure: Can increase blood pressure in adult patients. Periodically monitor blood pressure, especially in hypertensive patients. Mirabegron extended-release tablets are not recommended in patients with severe uncontrolled hypertension. (5.1)

- Urinary Retention in Patients With Bladder Outlet Obstruction and in Patients Taking Muscarinic Antagonist Drugs for Overactive Bladder: Administer with caution in these patients because of risk of urinary retention. (5.2)
- Angioedema: Angioedema of the face, lips, tongue, and/or larynx has been reported with mirabegron. (5.3, 6.2)

6 ADVERSE REACTIONS

Most commonly reported adverse reactions with mirabegron monotherapy in adult patients with OAB (> 2% and > placebo) were hypertension, nasopharyngitis, urinary tract infection, and headache. (6.1)

To report SUSPECTED ADVERSE REACTIONS, contact Lupin Pharmaceuticals, Inc. at 1-800-399-2561 or FDA at 1-800-FDA-1088 or www.fda.gov/medwatch.

7 DRUG INTERACTIONS

- Drugs Metabolized by CYP2D6: Mirabegron is a CYP2D6 inhibitor and, when used concomitantly with drugs metabolized by CYP2D6, especially narrow therapeutic index drugs, appropriate monitoring and possible dose adjustment of those drugs may be necessary. (5.4, 7.1, 12.3)
- Digoxin: When initiating a combination of mirabegron and digoxin, use the lowest dose of digoxin; monitor serum digoxin concentrations to titrate digoxin dose to desired clinical effect. (7.2, 12.3)

Pediatric use information is approved for Astellas Pharma Global Development, Inc.'s MYRBETRIQ (mirabegron extended-release tablets). However, due to Astellas Pharma Global Development, Inc.'s marketing exclusivity rights, this drug product is not labeled with that information.

FULL PRESCRIBING INFORMATION

1 INDICATIONS AND USAGE

1.1 Adult Overactive Bladder (OAB)

Mirabegron Extended-Release Tablets Monotherapy

Mirabegron extended-release tablets are indicated for the treatment of OAB in adult patients with symptoms of urge urinary incontinence, urgency, and urinary frequency.

Pediatric use information is approved for Astellas Pharma Global Development, Inc.'s MYRBETRIQ (mirabegron extended-release tablets). However, due to Astellas Pharma Global Development, Inc.'s marketing exclusivity rights, this drug product is not labeled with that information.

2 DOSAGE AND ADMINISTRATION

2.1 Important Dosage Information

Mirabegron extended-release tablets and mirabegron for extended-release oral suspension are two different products and they are not substitutable on a milligram-per milligram basis:

Select the recommended product (mirabegron extended-release tablets or mirabegron for extended-release oral suspension) based on the indication [see Indications and Usage (1)].

2.2 Recommended Dosage for Adult Patients with OAB

Mirabegron Extended-Release Tablets Monotherapy

The recommended starting dosage of mirabegron extended-release tablets is 25 mg orally once daily. If needed, increase to the maximum dosage of mirabegron extended-release tablets 50 mg orally once daily after 4 to 8 weeks. For administration instructions, see Dosage and Administration (2.7).

Pediatric use information is approved for Astellas Pharma Global Development, Inc.'s MYRBETRIQ (mirabegron extended-release tablets). However, due to Astellas Pharma Global Development, Inc.'s marketing exclusivity rights, this drug product is not labeled with that information

2.4 Recommended Dosage in Adult Patients with Renal or Hepatic Impairment

Dosage in Adults with Renal Impairment

The recommended dosage of mirabegron extended-release tablets (administered orally once daily) in adult patients with renal impairment is described in Table 2 [see Use in Specific Populations 8.6)]. For administration instructions, see Dosage and Administration (2.7).

Table 2: Mirabegron Extended-Release Tablets Recommended Dosage in Adult Patients with Renal Impairment (Administered Orally Once Daily)
Estimated GFR [Estimated GFR using the modification of diet in renal disease (MDRD) formula.] | Starting Dose | Maximum Dose
eGFR 30 to 89 mL/min/1.73 m^2 | 25 mg | 50 mg
eGFR 15 to 29 mL/min/1.73 m^2 | 25 mg | 25 mg
eGFR < 15 mL/min/1.73 m^2 or requiring dialysis | Not recommended

Dosage in Adults with Hepatic Impairment

The recommended dosage of mirabegron extended-release tablets (administered orally once daily) in adult patients with hepatic impairment is described in Table 3 [see Use in Specific Populations (8.7)]. For administration instructions, see Dosage and Administration (2.7).

Table 3: Mirabegron Extended-Release Tablets Recommended Dosage in Adult Patients with Hepatic Impairment (Administered Orally Once Daily)
Hepatic Impairment Classification | Starting Dose | Maximum Dose
Child-Pugh Class A (Mild hepatic impairment) | 25 mg | 50 mg
Child-Pugh Class B (Moderate hepatic impairment) | 25 mg | 25 mg
Child-Pugh Class C (Severe hepatic impairment) | Not Recommended

Pediatric use information is approved for Astellas Pharma Global Development, Inc.'s MYRBETRIQ (mirabegron extended-release tablets). However, due to Astellas Pharma Global Development, Inc.'s marketing exclusivity rights, this drug product is not labeled with that information.

2.7 Administration Instructions

Mirabegron Extended-Release Tablets

Adult patients:

Swallow mirabegron extended-release tablets whole with water. Do not chew, divide, or crush. Take with or without food.

2.8 Missed Dose

Instruct patients to take any missed doses as soon as they remember, unless more than 12 hours have passed since the missed dose. If more than 12 hours have passed, the missed dose can be skipped, and the next dose should be taken at the usual time.

3 DOSAGE FORMS AND STRENGTHS

Mirabegron extended-release tablets are supplied in two different strengths as described below:

- 25 mg White coloured, oval shaped, biconvex, film coated tablets debossed with "M25" on one side and "LU" on the other side.
- 50 mg Pale-yellow coloured, oval shaped, biconvex, film coated tablets debossed with "M50" on one side and "LU" on the other side.

4 CONTRAINDICATIONS

Mirabegron extended-release tablets are contraindicated in patients with known hypersensitivity reactions to mirabegron or any inactive ingredients of the tablet [see Adverse Reactions (6.1, 6.2)].

5 WARNINGS AND PRECAUTIONS

5.1 Increases in Blood Pressure

Increases in Blood Pressure in Adults

Mirabegron extended-release tablets can increase blood pressure. Periodic blood pressure determinations are recommended, especially in hypertensive patients. Mirabegron extended-release tablets are not recommended for use in patients with severe uncontrolled hypertension (defined as systolic blood pressure greater than or equal to 180 mm Hg and/or diastolic blood pressure greater than or equal to 110 mm Hg) [see Clinical Pharmacology (12.2)].

In two, randomized, placebo-controlled, healthy adult volunteer studies, mirabegron extended-release tablets were associated with dose-related increases in supine blood pressure. In these studies, at the maximum recommended dose of 50 mg, the mean maximum increase in systolic/diastolic blood pressure was approximately 3.5/1.5 mm Hg greater than placebo.

In contrast, in adult OAB patients in clinical trials, mirabegron extended-release tablets, taken as monotherapy, the mean increase in systolic and diastolic blood pressure at the maximum recommended mirabegron dose of 50 mg was approximately 0.5 to 1 mm Hg greater than placebo. Worsening of pre-existing hypertension was reported infrequently in patients taking mirabegron extended-release tablets.

Increases in Blood Pressure in Pediatric Patients 3 Years and Older

Mirabegron extended-release tablets can increase blood pressure in pediatric patients. Blood pressure increases may be larger in children (3 to less than 12 years of age) than in adolescents (12 to less than 18 years of age). Periodic blood pressure determinations are recommended. Mirabegron extended-release tablets is not recommended for use in pediatric patients with severe uncontrolled hypertension, defined as a systolic and/or diastolic blood pressure above the 99th percentile plus 5 mm Hg for age, sex, and stature using appropriate reference values.

Pediatric use information is approved for Astellas Pharma Global Development, Inc.'s MYRBETRIQ (mirabegron extended-release tablets). However, due to Astellas Pharma Global Development, Inc.'s marketing exclusivity rights, this drug product is not labeled with that information.

5.2 Urinary Retention in Patients with Bladder Outlet Obstruction and in Patients Taking Muscarinic Antagonist Medications for OAB

In patients taking mirabegron extended-release tablets, urinary retention has been reported to occur in patients with bladder outlet obstruction (BOO) and in patients taking muscarinic antagonist medications for the treatment of OAB. A controlled clinical safety study in patients with BOO did not demonstrate increased urinary retention in patients treated with mirabegron; however, mirabegron extended-release tablets should still be administered with caution to patients with clinically significant BOO. For example, monitor these patients for signs and symptoms of urinary retention. Mirabegron extended-release tablets should also be administered with caution to patients taking muscarinic antagonist medications for the treatment of OAB [see Clinical Pharmacology (12.2)].

5.3 Angioedema

Angioedema of the face, lips, tongue, and/or larynx has been reported with mirabegron extended-release tablets. In some cases, angioedema occurred after the first dose, however, cases have been reported to occur hours after the first dose or after multiple doses. Angioedema, associated with upper airway swelling, may be life-threatening. If involvement of the tongue, hypopharynx, or larynx occurs, promptly discontinue mirabegron extended-release tablets and provide appropriate therapy and/or measures necessary to ensure a patent airway [see Adverse Reactions (6.2)].

5.4 Patients Taking Drugs Metabolized by CYP2D6

Since mirabegron extended-release tablet is a moderate CYP2D6 inhibitor, the systemic exposure to CYP2D6 substrates is increased when coadministered with mirabegron extended-release tablet. Therefore, appropriate monitoring and dose adjustment may be necessary, especially with narrow therapeutic index drugs metabolized by CYP2D6 [see Drug Interactions (7.1) and Clinical Pharmacology (12.3)].

6 ADVERSE REACTIONS

The following adverse reactions are discussed in more detail in other sections of the labeling.

- Hypertension [see Warnings and Precautions (5.1)]
- Urinary Retention [see Warnings and Precautions (5.2)]
- Angioedema [see Warnings and Precautions (5.3)]

6.1 Clinical Trials Experience

Because clinical trials are conducted under widely varying conditions, adverse reaction rates observed in the clinical trials of a drug cannot be directly compared to rates in the clinical trials of another drug and may not reflect the rates observed in clinical practice.

Mirabegron Extended-Release Tablets Monotherapy for Adult OAB

In three, 12-week, double-blind, placebo-controlled, safety and efficacy studies in patients with OAB (Studies 1, 2, and 3), mirabegron extended-release tablets were evaluated for safety in 2736 patients [see Clinical Studies (14.1)]. Study 1 also included an active control. For the combined Studies 1, 2, and 3, 432 patients received mirabegron extended-release tablets 25 mg, 1375 received mirabegron extended-release tablets 50 mg, and 929 received mirabegron extended-release tablets 100 mg once daily. In these studies, the majority of the patients were Caucasian (94%) and female (72%) with a mean age of 59 years (range 18 to 95 years).

Mirabegron extended-release tablets were also evaluated for safety in 1632 patients who received mirabegron extended-release tablets 50 mg once daily (n=812 patients) or mirabegron extended-release tablets 100 mg (n=820 patients) in a 1-year, randomized, fixed-dose, double-blind, active-controlled, safety study in patients with OAB (Study 4). Of these patients, 731 received mirabegron extended-release tablets in a previous 12-week study. In Study 4, 1385 patients received mirabegron extended-release tablets continuously for at least 6 months, 1311 patients received mirabegron extended-release tablets for at least 9 months, and 564 patients received mirabegron extended-release tablets for at least 1 year.

The most frequent adverse events (0.2%) leading to discontinuation in Studies 1, 2, and 3 for the 25 mg or 50 mg dose were nausea, headache, hypertension, diarrhea, constipation, dizziness, and tachycardia.

Atrial fibrillation (0.2%) and prostate cancer (0.1%) were reported as serious adverse events by more than 1 patient and at a rate greater than placebo.

Table 8 lists the adverse reactions, derived from all adverse events, that were reported in Studies 1, 2, and 3 at an incidence greater than placebo and in 1% or more of patients treated with mirabegron extended-release tablets 25 mg or 50 mg once daily for up to 12 weeks. The most commonly reported adverse reactions (greater than 2% of mirabegron extended-release tablets patients and greater than placebo) were hypertension, nasopharyngitis, urinary tract infection, and headache.

Table 8: Percentages of Patients with Adverse Reactions, Derived from All Adverse Events, Exceeding Placebo Rate and Reported in ≥ 1% of OAB Patients Treated with Mirabegron Extended-Release Tablets, 25 mg or 50 mg Once Daily in Studies 1, 2, and 3
Adverse Reaction | Placebo (%) | Mirabegron Extended- Release Tablets 25 mg (%) | Mirabegron Extended- Release Tablets 50 mg (%)
Number of Patients | 1380 | 432 | 1375
Hypertension [Includes reports of blood pressure above the normal range, and BP increased from baseline, occurring predominantly in subjects with baseline hypertension.] | 7.6 | 11.3 | 7.5
Nasopharyngitis | 2.5 | 3.5 | 3.9
Urinary Tract Infection | 1.8 | 4.2 | 2.9
Headache | 3.0 | 2.1 | 3.2
Constipation | 1.4 | 1.6 | 1.6
Upper Respiratory Tract Infection | 1.7 | 2.1 | 1.5
Arthralgia | 1.1 | 1.6 | 1.3
Diarrhea | 1.3 | 1.2 | 1.5
Tachycardia | 0.6 | 1.6 | 1.2
Abdominal Pain | 0.7 | 1.4 | 0.6
Fatigue | 1.0 | 1.4 | 1.2

Other adverse reactions reported by less than 1% of patients treated with mirabegron extended-release tablets in Studies 1, 2, or 3 included:

Cardiac disorders:

Palpitations, blood pressure increased [see Clinical Pharmacology (12.2)]

Eye disorders:

Glaucoma [see Clinical Pharmacology (12.2)]

Gastrointestinal disorders:

Dyspepsia, gastritis, abdominal distension

Infections and Infestations:

Sinusitis, rhinitis

Investigations:

GGT increased, AST increased, ALT increased, LDH increased

Renal and urinary disorders:

Nephrolithiasis, bladder pain

Reproductive system and breast disorders:

Vulvovaginal pruritus, vaginal infection

Skin and subcutaneous tissue disorders:

Urticaria, leukocytoclastic vasculitis, rash, pruritus, purpura, lip edema

Table 9 lists the rates of the most commonly reported adverse reactions, derived from all adverse events in patients treated with mirabegron extended-release tablets 50 mg for up to 52 weeks in Study 4. The most commonly reported adverse reactions (>3% of mirabegron extended-release tablets patients) were hypertension, urinary tract infection, headache, and nasopharyngitis.

Table 9: Percentages of Patients with Adverse Reactions, Derived from All Adverse Events, Reported in > 2% of OAB Patients Treated with Mirabegron Extended-Release Tablets50 mg Once Daily in Study 4
Adverse Reaction | Mirabegron Extended-Release Tablets 50 mg (%) | Active Control (%)
Number of Patients | 812 | 812
Hypertension | 9.2 | 9.6
Urinary Tract Infection | 5.9 | 6.4
Headache | 4.1 | 2.5
Nasopharyngitis | 3.9 | 3.1
Back Pain | 2.8 | 1.6
Constipation | 2.8 | 2.7
Dry Mouth | 2.8 | 8.6
Dizziness | 2.7 | 2.6
Sinusitis | 2.7 | 1.5
Influenza | 2.6 | 3.4
Arthralgia | 2.1 | 2.0
Cystitis | 2.1 | 2.3

In Study 4, in patients treated with mirabegron extended-release tablets 50 mg once daily, adverse reactions leading to discontinuation reported by more than 2 patients and at a rate greater than active control included: constipation (0.9%), headache (0.6%), dizziness (0.5%), hypertension (0.5%), dry eyes (0.4%), nausea (0.4%), vision blurred (0.4%), and urinary tract infection (0.4%). Serious adverse events reported by at least 2 patients and exceeding active control included cerebrovascular accident (0.4%) and osteoarthritis (0.2%). Serum ALT/AST increased from baseline by greater than 10-fold in 2 patients (0.3%) taking mirabegron extended-release tablets 50 mg; and these markers subsequently returned to baseline while both patients continued mirabegron extended-release tablets.

In Study 4, serious adverse events of neoplasm were reported by 0.1%, 1.3%, and 0.5% of patients treated with mirabegron extended-release tablets 50 mg, mirabegron extended-release tablets 100 mg, and active control once daily, respectively. Neoplasms reported by 2 patients treated with mirabegron extended-release tablets 100 mg included breast cancer, lung neoplasm malignant, and prostate cancer. A causal relationship between mirabegron and these reported neoplasms has not been established.

In a separate clinical study in Japan, a single case was reported as Stevens-Johnson syndrome with increased serum ALT, AST, and bilirubin in a patient taking mirabegron extended-release tablets 100 mg as well as an herbal medication (Kyufu Gold).

Pediatric use information is approved for Astellas Pharma Global Development, Inc.'s MYRBETRIQ (mirabegron extended-release tablets). However, due to Astellas Pharma Global Development, Inc.'s marketing exclusivity rights, this drug product is not labeled with that information.

6.2 Postmarketing Experience

The following adverse reactions have been identified during post-approval use of mirabegron extended-release tablets. Because these reactions are reported voluntarily from a population of uncertain size, it is not always possible to reliably estimate their frequency or establish a causal relationship to drug exposure. The following events have been reported in association with mirabegron use in worldwide postmarketing experience:

Cardiac disorders:

Atrial fibrillation

Gastrointestinal disorders:

Nausea, constipation, diarrhea

Nervous system disorders:

Dizziness, headache

There have been postmarketing reports of confusion, hallucinations, insomnia, and anxiety in patients taking mirabegron. The majority of these patients had pre-existing medical conditions or concomitant medications that may cause confusion, hallucinations, insomnia, and anxiety. A causal relationship between mirabegron and these disorders has not been established.

Skin and subcutaneous tissue disorders:

Angioedema of the face, lips, tongue, and larynx, with or without respiratory symptoms [see Warnings and Precautions (5.3)]; pruritus

Renal and urinary disorders:

Urinary retention [see Warnings and Precautions (5.2)]

7 DRUG INTERACTIONS

Drug interaction studies were conducted in adult patients to investigate the effect of coadministered drugs on the pharmacokinetics of mirabegron and the effect of mirabegron on the pharmacokinetics of coadministered drugs (e.g., ketoconazole, rifampin, solifenacin succinate, tamsulosin, and oral contraceptives) [see Clinical Pharmacology (12.3)]. No dose adjustment is recommended when these drugs are coadministered with mirabegron.

The following are drug interactions for which monitoring is recommended:

7.1 Drugs Metabolized by CYP2D6

Since mirabegron is a moderate CYP2D6 inhibitor, the systemic exposure of drugs metabolized by CYP2D6 enzyme is increased when coadministered with mirabegron. Therefore, appropriate monitoring and dose adjustment may be necessary when mirabegron extended-release tablet is coadministered with these drugs, especially with narrow therapeutic index CYP2D6 substrates [see Warnings and Precautions (5.4) and Clinical Pharmacology (12.3)].

7.2 Digoxin

When given in combination, 100 mg mirabegron increased mean digoxin Cmax from 1.01 to 1.3 ng/mL (29%) and AUC from 16.7 to 19.3 ng.h/mL (27%). For patients who are initiating a combination of mirabegron and digoxin, the lowest dose for digoxin should initially be considered. Serum digoxin concentrations should be monitored and used for titration of the digoxin dose to obtain the desired clinical effect [see Clinical Pharmacology (12.3)].

7.3 Warfarin

The mean Cmax of S- and R-warfarin was increased by approximately 4% and AUC by approximately 9% when administered as a single dose of 25 mg after multiple doses of 100 mg mirabegron. Following a single dose administration of 25 mg warfarin, mirabegron had no effect on the warfarin pharmacodynamic endpoints such as International Normalized Ratio (INR) and prothrombin time. However, the effect of mirabegron on multiple doses of warfarin and on warfarin pharmacodynamic end points such as INR and prothrombin time has not been fully investigated [see Clinical Pharmacology (12.3)].

8 USE IN SPECIFIC POPULATIONS

8.1 Pregnancy

Risk Summary

There are no studies with the use of mirabegron in pregnant women or adolescents to inform a drug-associated risk of major birth defects, miscarriages, or adverse maternal or fetal outcomes. Mirabegron administration to pregnant animals during organogenesis resulted in reversible skeletal variations (in rats) at 22-fold (via AUC) the maximum recommended human dose (MRHD) of 50 mg/day and decreased fetal body weights (in rabbits) at 14-fold the MRHD. At maternally-toxic exposures in rats (96-fold), decreased fetal weight and increased fetal mortality were observed and, in rabbits (36-fold), cardiac findings (fetal cardiomegaly and fetal dilated aortae) were observed [see Data].

The estimated background risks of major birth defects and miscarriage for the indicated populations are unknown. In the U.S. general population, the estimated background risk of major birth defects or miscarriage in clinically recognized pregnancies are 2 to 4% and 15 to 20%, respectively.

Data

Animal Data:

No embryo-fetal lethality or morphological fetal developmental abnormalities were produced in pregnant rats following daily oral administration of mirabegron during the period of organogenesis (Days 7 to 17 of gestation) at 0, 10, 30, 100, or 300 mg/kg, doses which were associated with systemic exposures (AUC) 0, 1, 6, 22, and 96-fold the MRHD. Skeletal variations (wavy ribs, delayed ossification) were observed in fetuses at doses 22-fold the systemic exposure at the MRHD and were reversible during development. Exposures 96-fold the MRHD were maternally-toxic (mortality, decreased body weight gain) and associated with fetal growth reduction.

Pregnant rabbits were treated with daily oral doses of mirabegron at 0, 3, 10, or 30 mg/kg/day during the period of organogenesis (Days 6 to 20 of gestation), which resulted in plasma exposures that were 0, 1, 14, or 36-fold the MRHD based on AUC. At 10 mg/kg/day (14-fold the MRHD) and higher, fetal body weights were reduced. At 30 mg/kg/day, maternal toxicity (increased heart rate, mortality, reduced body weight gain, reduced food consumption) occurred, and fetal deaths, fetal cardiomegaly and fetal dilated aortae were observed at systemic exposure levels (AUC) 36-fold the MRHD.

In a pre- and postnatal developmental study, rats were treated with daily oral doses of mirabegron at 0, 10, 30, or 100 mg/kg/day (0, 1, 6, or 22-fold the MRHD) from day 7 of gestation until day 20 after birth. Decreased maternal body weight was observed along with decreased pup survival in the first few days after birth (92.7% survival) compared to the control group (98.8% survival), at 100 mg/kg/day (22-fold the MRHD). Pup body weight gain was reduced until postnatal day 7 but not further affected throughout the remainder of the lactation period. In utero and lactational exposure did not affect developmental milestones, behavior, or fertility of offspring. No effects were observed at 30 mg/kg/day.

8.2 Lactation

Risk Summary

There are no data on the presence of mirabegron in human milk, the effects on the breastfed child, or the effects on milk production. Mirabegron-related material was present in rat milk and in the stomach of nursing pups following administrations of a single 10 mg/kg oral dose of ^14C-labeled mirabegron to lactating rats. When a drug is present in animal milk, it is likely that the drug will be present in human milk.

The developmental and health benefits of breastfeeding should be considered along with the mother's clinical need for mirabegron extended-release tablets and any potential adverse effects on the breastfed child from mirabegron or from the underlying maternal condition.

8.4 Pediatric Use

Increased mean systolic and diastolic blood pressures with use of mirabegron extended-release-tablets occurred in patients less than 12 years of age with larger increases in patients younger than 8 years of age.

Pediatric use information is approved for Astellas Pharma Global Development, Inc.'s MYRBETRIQ (mirabegron extended-release tablets). However, due to Astellas Pharma Global Development, Inc.'s marketing exclusivity rights, this drug product is not labeled with that information.

8.5 Geriatric Use

Of 5648 patients who received mirabegron extended-release tablets monotherapy in the phase 2 and 3 studies for OAB, 2029 (35.9%) were 65 years of age or older, and 557 (9.9%) were 75 years of age or older. No overall differences in safety or effectiveness were observed between patients younger than 65 years of age and those 65 years of age or older in these studies.

8.6 Renal Impairment

Mirabegron extended-release tablets have not been studied in patients with End-Stage Renal Disease (eGFR <15 mL/min/1.73 m^2) or patients requiring hemodialysis and, therefore, is not recommended for use in these patient populations. No dose adjustment is necessary in patients with mild or moderate renal impairment (eGFR 30 to 89 mL/min/1.73 m^2).

In adult patients with severe renal impairment (eGFR 15 to 29 mL/min/1.73 m^2), the daily dose of mirabegron extended-release tablets should not exceed 25 mg [see Clinical Pharmacology (12.3)].

Pediatric use information is approved for Astellas Pharma Global Development, Inc.'s MYRBETRIQ (mirabegron extended-release tablets). However, due to Astellas Pharma Global Development, Inc.'s marketing exclusivity rights, this drug product is not labeled with that information.

8.7 Hepatic Impairment

Mirabegron extended-release tablets have not been studied in patients with severe hepatic impairment (Child-Pugh Class C) and, therefore, is not recommended for use in this patient population. No dose adjustment is necessary in patients with mild hepatic impairment (Child-Pugh Class A).

In adult patients with moderate hepatic impairment (Child-Pugh Class B), the daily dose of mirabegron extended-release tablets should not exceed 25 mg [see Clinical Pharmacology (12.3)].

Pediatric use information is approved for Astellas Pharma Global Development, Inc.'s MYRBETRIQ (mirabegron extended-release tablets). However, due to Astellas Pharma Global Development, Inc.'s marketing exclusivity rights, this drug product is not labeled with that information.

10 OVERDOSAGE

Mirabegron has been administered to healthy volunteers at single doses up to 400 mg. At this dose, adverse events reported included palpitations (1 of 6 subjects) and increased pulse rate exceeding 100 beats per minute (bpm) (3 of 6 subjects). Multiple doses of mirabegron up to 300 mg daily for 10 days showed increases in pulse rate and systolic blood pressure when administered to healthy volunteers. Treatment for overdosage should be symptomatic and supportive. In the event of overdosage, pulse rate, blood pressure and ECG monitoring is recommended.

11 DESCRIPTION

Mirabegron extended-release tablet for oral use is a beta-3 adrenergic agonist. The chemical name of mirabegron is 2-(2-Amino-1,3-thiazol-4-yl)-N-[4-(2-{([(2R)-2-hydroxy-2-phenylethyl] amino}ethyl)phenyl] acetamide having an empirical formula of C21H24N4O2S and a molecular weight of 396.51. The structural formula of mirabegron is:

Mirabegron is an off-white to light yellow colored powder. It is practically insoluble in water. It is soluble in methanol and dimethyl sulfoxide.

Each mirabegron extended-release tablet for oral use contains either 25 mg or 50 mg of mirabegron and the following inactive ingredients: butylated hydroxytoluene, D&C Yellow No.10 Aluminum Lake, FD&C Yellow No. 6, hydroxy propyl cellulose, hypromellose, magnesium stearate, microcrystalline cellulose, polyethylene glycol, polyethylene oxide, titanium dioxide, triacetin.

12 CLINICAL PHARMACOLOGY

12.1 Mechanism of Action

Mirabegron is an agonist of the human beta-3 adrenergic receptor (AR) as demonstrated by in vitro laboratory experiments using the cloned human beta-3 AR. Mirabegron relaxes the detrusor smooth muscle during the storage phase of the urinary bladder fill-void cycle by activation of beta-3 AR which increases bladder capacity. Although mirabegron showed very low intrinsic activity for cloned human beta-1 AR and beta-2 AR, results in humans indicate that beta-1 AR stimulation occurred at a mirabegron dose of 200 mg.

12.2 Pharmacodynamics

Urodynamics

The effects of mirabegron on maximum urinary flow rate and detrusor pressure at maximum flow rate were assessed in a urodynamic study consisting of 200 male patients with lower urinary tract symptoms (LUTS) and BOO. Administration of mirabegron once daily for 12 weeks did not adversely affect the mean maximum flow rate or mean detrusor pressure at maximum flow rate in this study. Nonetheless, mirabegron should be administered with caution to patients with clinically significant BOO [see Warnings and Precautions (5.2)].

Cardiac Electrophysiology

The effect of multiple doses of mirabegron 50 mg, 100 mg, and 200 mg (four times the maximum recommended dose) once daily on QTc interval was evaluated in a randomized, placebo- and active-controlled (moxifloxacin 400 mg), four-treatment arm, parallel crossover study in 352 healthy subjects. In a study with demonstrated ability to detect small effects, the upper bound of the one-sided 95% confidence interval for the largest placebo-adjusted, baseline-corrected QTc based on individual correction method (QTcI) was below 10 msec. For the 50 mg mirabegron dose group (the maximum approved dosage), the mean difference from placebo on QTcI interval at 4 to 5 hours post-dose was 3.7 msec (upper bound of the 95% CI 5.1 msec).

For the mirabegron 100 mg and 200 mg dose groups (dosages greater than the maximum approved dose and resulting in substantial multiples of the anticipated maximum blood levels at 50 mg), the mean differences from placebo in QTcI interval at 4 to 5 hours post dose were 6.1 msec (upper bound of the 95% CI 7.6 msec) and 8.1 msec (upper bound of the 95% CI 9.8 msec), respectively. At the mirabegron 200 mg dose, in females, the mean effect was 10.4 msec (upper bound of the 95% CI 13.4 msec).

In this thorough QT study, mirabegron increased heart rate on ECG in a dose-dependent manner. Maximum mean increases from baseline in heart rate for the 50 mg, 100 mg, and 200 mg dose groups compared to placebo were 6.7 bpm, 11 bpm, and 17 bpm, respectively. In the clinical efficacy and safety studies, the change from baseline in mean pulse rate for mirabegron 50 mg was approximately 1 bpm. In this thorough QT study, mirabegron also increased blood pressure in a dose-dependent manner (see Effects on Blood Pressure).

Effects on Blood Pressure

In a study of 352 healthy subjects assessing the effect of multiple daily doses of 50 mg, 100 mg, and 200 mg (four times the maximum recommended dose) of mirabegron for 10 days on the QTc interval, the maximum mean increase in supine systolic blood pressure (SBP)/ diastolic blood pressure (DBP) at the maximum recommended dose of 50 mg was approximately 4.0/1.6 mm Hg greater than placebo [see Warnings and Precautions (5.1)]. The 24-hour average increases in SBP compared to placebo were 3.0, 5.5, and 9.7 mm Hg at mirabegron doses of 50 mg, 100 mg, and 200 mg, respectively. Increases in DBP were also dose-dependent, but were smaller than SBP.

In another study in 96 healthy subjects to assess the impact of age on pharmacokinetics of multiple daily doses of 50 mg, 100 mg, 200 mg, and 300 mg (six times the maximum recommended dose) of mirabegron for 10 days, SBP also increased in a dose-dependent manner. The mean maximum increases in SBP were approximately 2.5, 4.5, 5.5, and 6.5 mm Hg for mirabegron exposures associated with doses of 50 mg, 100 mg, 200 mg, and 300 mg, respectively.

In three, 12-week, double-blind, placebo-controlled, safety and efficacy studies (Studies 1, 2, and 3) in patients with OAB receiving mirabegron 25 mg, 50 mg, or 100 mg (two times the maximum recommended dose) once daily, mean increases in SBP/DBP compared to placebo of approximately 0.5 to 1 mm Hg were observed. Morning SBP increased by at least 15 mm Hg from baseline in 5.3%, 5.1%, and 6.7% of placebo, mirabegron 25 mg and mirabegron 50 mg patients, respectively. Morning DBP increased by at least 10 mm Hg in 4.6%, 4.1%, and 6.6% of placebo, mirabegron 25 mg, and mirabegron 50 mg patients, respectively. Both SBP and DBP increases were reversible upon discontinuation of treatment.

Effect on Intraocular Pressure (IOP)

Mirabegron 100 mg once daily did not increase IOP in healthy subjects after 56 days of treatment. In a phase 1 study assessing the effect of mirabegron on IOP using Goldmann applanation tonometry in 310 healthy subjects, a dose of mirabegron 100 mg was non-inferior to placebo for the primary endpoint of the treatment difference in mean change from baseline to day 56 in subject average IOP; the upper bound of the two-sided 95% CI of the treatment difference between mirabegron 100 mg and placebo was 0.3 mm Hg.

12.3 Pharmacokinetics

Absorption

Mirabegron Extended-Release Tablets Monotherapy for Adult OAB:

After oral administration of mirabegron in healthy volunteers, mirabegron was absorbed to reach maximum plasma concentrations (Cmax) at approximately 3.5 hours. The absolute bioavailability increased from 29% at a dose of 25 mg to 35% at a dose of 50 mg. Mean Cmax and AUC increased more than dose proportionally. This relationship was more apparent at doses above 50 mg. In the overall population of males and females, a 2-fold increase in dose from 50 mg to 100 mg mirabegron increased Cmax and AUCtau by approximately 2.9-and 2.6-fold, respectively, whereas a 4-fold increase in dose from 50 to 200 mg mirabegron increased Cmax and AUCtau by approximately 8.4-and 6.5-fold. Steady-state concentrations were achieved within 7 days of once daily dosing with mirabegron. After once daily administration, plasma exposure of mirabegron at steady-state was approximately double that seen after a single dose.

Effect of Food:

Mirabegron Extended-Release Tablets Monotherapy for Adult OAB:

There were no clinically significant differences in mirabegron pharmacokinetics when administered with or without food in adult patients.

Distribution

Mirabegron Extended-Release Tablets Monotherapy for Adult OAB:

Mirabegron is extensively distributed in the body. The volume of distribution at steady-state (Vss) is approximately 1670 L following intravenous administration. Mirabegron is bound (approximately 71%) to human plasma proteins, and shows moderate affinity for albumin and alpha-1 acid glycoprotein. Mirabegron distributes to erythrocytes. Based on an in vitro study, erythrocyte concentrations of ^14C-mirabegron were about 2-fold higher than in plasma.

Elimination

Mirabegron Extended-Release Tablets Monotherapy for Adult OAB:

The terminal elimination half-life (t1/2) of mirabegron is approximately 50 hours in patients.

Metabolism

Mirabegron is metabolized via multiple pathways involving dealkylation, oxidation, (direct) glucuronidation, and amide hydrolysis. Mirabegron is the major circulating component following a single dose of ^14C-mirabegron. Two major metabolites were observed in human plasma and are phase 2 glucuronides representing 16% and 11% of total exposure, respectively. These metabolites are not pharmacologically active toward beta-3 adrenergic receptor. Although, in vitro studies suggest a role for CYP2D6 and CYP3A4 in the oxidative metabolism of mirabegron, in vivo results indicate that these isozymes play a limited role in the overall elimination. In healthy subjects who were genotypically poor metabolizers of CYP2D6, mean Cmax and AUCtau were approximately 16% and 17% higher than in extensive metabolizers of CYP2D6, respectively. In vitro and ex vivo studies have shown the involvement of butylcholinesterase, uridine diphospho-glucuronosyltransferases (UGT), and possibly alcohol dehydrogenase in the metabolism of mirabegron, in addition to CYP3A4 and CYP2D6.

Excretion

Mirabegron Extended-Release Tablets Monotherapy for Adult OAB:

Total body clearance (CLtot) from plasma is approximately 57 L/h following intravenous administration. Renal clearance (CLR) is approximately 13 L/h, which corresponds to nearly 25% of CLtot. Renal elimination of mirabegron is primarily through active tubular secretion along with glomerular filtration. The urinary elimination of unchanged mirabegron is dose-dependent and ranges from approximately 6.0% after a daily dose of 25 mg to 12.2% after a daily dose of 100 mg. Following the administration of 160 mg ^14C-mirabegron solution to healthy volunteers, approximately 55% of the radioactivity dose was recovered in the urine and 34% in the feces. Approximately 25% of unchanged mirabegron was recovered in urine and 0% in feces.

Specific Populations

Geriatric Patients:

The Cmax and AUC of mirabegron following multiple oral doses in elderly volunteers (≥ 65 years) were similar to those in younger volunteers (18 to 45 years) [see Use in Specific Populations (8.5)].

Gender:

Mirabegron Extended-Release Tablets Monotherapy for Adult OAB

The Cmax and AUC of mirabegron were approximately 40% to 50% higher in females than in males. When corrected for differences in body weight, the mirabegron systemic exposure was 20% to 30% higher in females compared to males.

Race:

The pharmacokinetics of mirabegron were comparable between Caucasians and African-American Blacks. Cross studies comparison showed that the exposure in Japanese subjects were higher than that in North American subjects. However, when the Cmax and AUC were normalized for dose and body weight, the difference was smaller.

Patients with Renal Impairment:

Following single-dose administration of 100 mg mirabegron in adult volunteers with mild renal impairment (eGFR 60 to 89 mL/min/1.73 m^2 as estimated by MDRD), mean mirabegron Cmax and AUC were increased by 6% and 31% relative to adult volunteers with normal renal function. In adult volunteers with moderate renal impairment (eGFR 30 to 59 mL/min/1.73 m^2), Cmax and AUC were increased by 23% and 66%, respectively. In adult volunteers with severe renal impairment (eGFR 15 to 29 mL/min/1.73 m^2), mean Cmax and AUC values were 92% and 118% higher compared to healthy subjects with normal renal function. Mirabegron has not been studied in adult patients with End-Stage Renal Disease (ESRD) (eGFR less than 15 mL/min/1.73 m^2) or adult patients requiring dialysis.

Patients with Hepatic Impairment:

Following single-dose administration of 100 mg mirabegron in adult volunteers with mild hepatic impairment (Child- Pugh Class A), mean mirabegron Cmax and AUC were increased by 9% and 19%, relative to adult volunteers with normal hepatic function. In adult volunteers with moderate hepatic impairment (Child-Pugh Class B), mean Cmax and AUC values were 175% and 65% higher. Mirabegron has not been studied in adult patients with severe hepatic impairment (Child-Pugh Class C).

Drug Interaction Studies

In Vitro Studies:

Effect of Other Drugs on Mirabegron

Mirabegron is transported and metabolized through multiple pathways. Mirabegron is a substrate for CYP3A4, CYP2D6, butyrylcholinesterase, UGT, the efflux transporter P-glycoprotein (P-gp), and the influx organic cation transporters (OCT) OCT1, OCT2, and OCT3. Sulfonylurea hypoglycemic agents glibenclamide (a CYP3A4 substrate), gliclazide (a CYP2C9 and CYP3A4 substrate), and tolbutamide (a CYP2C9 substrate) did not affect the in vitro metabolism of mirabegron.

Effect of Mirabegron on Other Drugs

Studies of mirabegron using human liver microsomes and recombinant human CYP enzymes showed that mirabegron is a moderate and time-dependent inhibitor of CYP2D6 and a weak inhibitor of CYP3A. Mirabegron is unlikely to inhibit the metabolism of coadministered drugs metabolized by the following cytochrome P450 enzymes: CYP1A2, CYP2B6, CYP2C8, CYP2C9, CYP2C19 and CYP2E1 because mirabegron did not inhibit the activity of these enzymes at clinically relevant concentrations. Mirabegron did not induce CYP1A2 or CYP3A. Mirabegron inhibited P-gp-mediated drug transport at high concentrations. Mirabegron is predicted not to cause clinically relevant inhibition of OCT-mediated drug transport. Mirabegron did not affect the metabolism of glibenclamide or tolbutamide.

In Vivo Studies:

Mirabegron Extended-Release Tablets Monotherapy for Adult OAB

The effect of coadministered drugs on the pharmacokinetics of mirabegron and the effect of mirabegron on the pharmacokinetics of coadministered drugs was studied after single and multiple doses of mirabegron. Most drug-drug interactions (DDI) were studied using mirabegron 100 mg extended-release tablets. However, interaction studies of mirabegron with metoprolol and with metformin were studied using mirabegron 160 mg immediate-release (IR) tablets.

The effect of ketoconazole, rifampicin, solifenacin succinate, tamsulosin, and metformin on systemic mirabegron exposure is shown in Figure 1.

The effect of mirabegron on metoprolol, desipramine, combined oral contraceptive-COC (ethinyl estradiol-EE, levonorgestrel-LNG), solifenacin succinate, digoxin, warfarin, tamsulosin, and metformin is shown in Figure 2.

In these studies, the largest increase in mirabegron systemic exposure was seen in the ketoconazole DDI study. As a potent CYP3A4 inhibitor, ketoconazole increased mirabegron Cmax by 45% and mirabegron AUC by 80% after multiple dose administration of 400 mg of ketoconazole for 9 days prior to the administration of a single dose of 100 mg mirabegron in 23 male and female healthy subjects.

As a moderate CYP2D6 inhibitor, mirabegron increased the systemic exposure to metoprolol and desipramine:

- Mirabegron increased the Cmax of metoprolol by 90% and metoprolol AUC by 229% after multiple doses of 160 mg mirabegron IR tablets once daily for 5 days and a single dose of 100 mg metoprolol tablet in 12 healthy male subjects administered before and concomitantly with mirabegron.
- Mirabegron increased the Cmax of desipramine by 79% and desipramine AUC by 241% after multiple dose administration of 100 mg mirabegron once daily for 18 days and a single dose of 50 mg desipramine before and concomitantly with mirabegron in 28 male and female healthy subjects.

Figures 1 and 2 show the magnitude of these interactions on the pharmacokinetic parameters and the recommendations for dose adjustment, if any:

Figure 1: The Effect of Coadministered Drugs on Exposure of Mirabegron Extended-Release Tablets and Dose Recommendation

(1) Although no dose adjustment is recommended with solifenacin succinate or tamsulosin based on the lack of pharmacokinetic interaction, mirabegron extended-release tablets should be administered with caution to patients taking muscarinic antagonist medications for the treatment of OAB and in patients with clinically significant BOO because of the risk of urinary retention [see Warnings and Precautions (5.2)].

Figure 2: The Effect of Mirabegron Extended-Release Tablets on Exposure of Coadministered Medication

(1) Since mirabegron is a moderate CYP2D6 inhibitor, the systemic exposure to CYP2D6 substrates such as metoprolol and desipramine is increased when coadministered with mirabegron. Therefore, appropriate monitoring and dose adjustment may be necessary, especially with narrow therapeutic index CYP2D6 substrates, such as thioridazine, flecainide, and propafenone [see Warnings and Precautions (5.4) and Drug Interactions (7.1)].

(2) For patients who are initiating a combination of mirabegron and digoxin, the lowest dose for digoxin should initially be prescribed. Serum digoxin concentrations should be monitored and used for titration of the digoxin dose to obtain the desired clinical effect [see Drug Interactions (7.2)].

(3) Warfarin was administered as a single 25 mg dose of the racemate (a mixture of R-warfarin and S-warfarin). Based on this single-dose study, mirabegron had no effect on the warfarin pharmacodynamic endpoints such as INR and prothrombin time. However, the effect of mirabegron on multiple doses of warfarin and on warfarin pharmacodynamic end points such as INR and prothrombin time has not been fully investigated [see Drug Interactions (7.3)].

(4) Although no dose adjustment is recommended with solifenacin succinate or tamsulosin based on the lack of pharmacokinetic interaction, mirabegron extended-release tablets should be administered with caution to patients taking muscarinic antagonist medications for the treatment of OAB and in BOO because of the risk of urinary retention [see Warnings and Precautions (5.2)].

Pediatric use information is approved for Astellas Pharma Global Development, Inc.'s MYRBETRIQ (mirabegron extended-release tablets). However, due to Astellas Pharma Global Development, Inc.'s marketing exclusivity rights, this drug product is not labeled with that information.

13 NONCLINICAL TOXICOLOGY

13.1 Carcinogenesis, Mutagenesis, Impairment of Fertility

Carcinogenicity

Long-term carcinogenicity studies were conducted in rats and mice dosed orally with mirabegron for two years. Male rats were dosed at 0, 12.5, 25, or 50 mg/kg/day and female rats and both sexes of mice were dosed at 0, 25, 50, or 100 mg/kg/day. Mirabegron showed no carcinogenic potential at systemic exposures (AUC) 38 to 45-fold higher than the MRHD in rats and 21 to 38-fold higher than the MRHD in mice than the human systemic exposure at the 50 mg dose.

Mutagenesis

Mirabegron was not mutagenic in the Ames bacterial reverse mutation assay, did not induce chromosomal aberrations in human peripheral blood lymphocytes at concentrations that were not cytotoxic, and was not clastogenic in the rat micronucleus assay.

Impairment of Fertility

Fertility studies in rats showed that mirabegron had no effect on either male or female fertility at non-lethal doses up to 100 mg/kg/day. Systemic exposures (AUC) at 100 mg/kg in female rats was estimated to be 22-fold the MRHD in women and 93-fold the MRHD in men.

14 CLINICAL STUDIES

14.1 Mirabegron Extended-Release Tablets Monotherapy for Adult OAB

Mirabegron extended-release tablets were evaluated in three, 12-week, double-blind, randomized, placebo-controlled, parallel group, multicenter clinical trials in patients with overactive bladder with symptoms of urge urinary incontinence, urgency, and urinary frequency (Studies 1, 2, and 3). Entry criteria required that patients had symptoms of overactive bladder for at least 3 months duration, at least 8 micturitions per day, and at least 3 episodes of urgency with or without incontinence over a 3-day period. The majority of patients were Caucasian (94%) and female (72%) with a mean age of 59 years (range 18 to 95 years). The population included both naïve patients who had not received prior muscarinic antagonist pharmacotherapy for overactive bladder (48%) and those who had received prior muscarinic antagonist pharmacotherapy for OAB (52%).

In Study 1 (NCT00689104), patients were randomized to placebo, mirabegron extended-release tablets 50 mg, mirabegron extended-release tablets 100 mg, or an active control once daily. In Study 2 (NCT00662909), patients were randomized to placebo, mirabegron extended-release tablets 50 mg or mirabegron extended-release tablets 100 mg once daily. In Study 3 (NCT00912964), patients were randomized to placebo, mirabegron extended-release tablets 25 mg or mirabegron extended-release tablets 50 mg once daily.

The co-primary efficacy endpoints in all 3 trials were (1) change from baseline to end of treatment (Week 12) in mean number of incontinence episodes per 24 hours and (2) change from baseline to end of treatment (Week 12) in mean number of micturitions per 24 hours, based on a 3-day micturition diary. An important secondary endpoint was the change from baseline to end of treatment (Week 12) in mean volume voided per micturition.

Results for the co-primary endpoints and mean volume voided per micturition from Studies 1, 2, and 3 are shown in Table 13.

Table 13: Mean Baseline and Change from Baseline at Week 12* for Incontinence Episodes, Micturition Frequency, and Volume Voided per Micturition in Patients with Overactive Bladder in Studies 1, 2, and 3
Parameter | Study 1 |  | Study 2 |  | Study 3
 | Placebo | Mirabegron Extended-Release Tablets 50 mg | Placebo | Mirabegron Extended-Release Tablets 50 mg | Placebo | Mirabegron Extended-Release Tablets 25 mg | Mirabegron Extended-Release Tablets 50 mg
Number of Incontinence Episodes per 24 Hours [For incontinence episodes per 24 hours, the analysis population is restricted to patients with at least 1 episode of incontinence at baseline.]
n | 291 | 293 | 325 | 312 | 262 | 254 | 257
Baseline (mean) | 2.67 | 2.83 | 3.03 | 2.77 | 2.43 | 2.65 | 2.51
Change from baseline (adjusted mean [Least squares mean adjusted for baseline, gender, and geographical region.]) | -1.17 | -1.57 | -1.13 | -1.47 | -0.96 | -1.36 | -1.38
Difference from placebo (adjusted mean) | - | -0.41 | - | -0.34 | - | -0.40 | -0.42
95% Confidence Interval | - | (-0.72, -0.09) | - | (-0.66, -0.03) | - | (-0.74, -0.06) | (-0.76, -0.08)
p-value |  | 0.003 [Statistically significantly superior compared to placebo at the 0.05 level with multiplicity adjustment] |  | 0.026 |  | 0.005 | 0.001
Number of Micturitions per 24 Hours
n | 480 | 473 | 433 | 425 | 415 | 410 | 426
Baseline (mean) | 11.71 | 11.65 | 11.51 | 11.80 | 11.48 | 11.68 | 11.66
Change from baseline (adjusted mean) | -1.34 | -1.93 | -1.05 | -1.66 | -1.18 | -1.65 | -1.60
Difference from placebo (adjusted mean) | - | -0.60 | - | -0.61 | - | -0.47 | -0.42
95% Confidence Interval | - | (-0.90, -0.29) | - | (-0.98, -0.24) | - | (-0.82, -0.13) | (-0.76, -0.08)
p-value |  | < 0.001 |  | 0.001 |  | 0.007 | 0.015
Volume Voided (mL) per Micturition
n | 480 | 472 | 433 | 424 | 415 | 410 | 426
Baseline (mean) | 156.7 | 161.1 | 157.5 | 156.3 | 164.0 | 165.2 | 159.3
Change from baseline (adjusted mean) | 12.3 | 24.2 | 7.0 | 18.2 | 8.3 | 12.8 | 20.7
Difference from placebo (adjusted mean) | - | 11.9 | - | 11.1 | - | 4.6 | 12.4
95% Confidence Interval | - | (6.3, 17.4) | - | (4.4, 17.9) | - | (-1.6, 10.8) | (6.3, 18.6)
p-value |  | < 0.001 |  | 0.001 |  | 0.15 | < 0.001
*Week 12 is last observation on treatment

Mirabegron extended-release tablets 25 mg was effective in treating the symptoms of OAB within 8 weeks and mirabegron extended-release tablets 50 mg was effective in treating the symptoms of OAB within 4 weeks. Efficacy of both 25 mg and 50 mg doses of mirabegron extended-release tablet was maintained through the 12-week treatment period.

Figures 3 through 8 show the co-primary endpoints, mean change from baseline (BL) over time in number of incontinence episodes per 24 hours, and mean change from baseline over time in number of micturitions per 24 hours, in Studies 1, 2, and 3.

Figure 3: Mean (SE) Change from Baseline in Mean Number of Incontinence Episodes per 24 Hours – Study 1

Figure 4: Mean (SE) Change from Baseline in Mean Number of Micturitions per 24 Hours - Study 1

Figure 5: Mean (SE) Change from Baseline in Mean Number of Incontinence Episodes per 24 Hours - Study 2

Figure 6: Mean (SE) Change from Baseline in Mean Number of Micturitions per 24 Hours - Study 2

Figure 7: Mean (SE) Change from Baseline in Mean Number of Incontinence Episodes per 24 Hours - Study 3

Figure 8: Mean (SE) Change from Baseline in Mean Number of Micturitions per 24 Hours -Study 3

Pediatric use information is approved for Astellas Pharma Global Development, Inc.'s MYRBETRIQ (mirabegron extended-release tablets). However, due to Astellas Pharma Global Development, Inc.'s marketing exclusivity rights, this drug product is not labeled with that information.

16 HOW SUPPLIED/STORAGE AND HANDLING

16.1 Mirabegron Extended-Release Tablets

Mirabegron extended-release tablets are supplied as oval, film-coated, extended-release tablets, available in bottles as follows:

Strength | 25 mg | 50 mg
Color | White | Pale-yellow
Debossed | M25, LU | M50, LU
Bottle of 30 | NDC 68180-151-06 | NDC 68180-152-06
Bottle of 90 | NDC 68180-151-09 | NDC 68180-152-09

Store and Dispense

Store at 25°C (77°F) with excursions permitted from 15° to 30°C (59° to 86°F). [see USP Controlled Room Temperature].

17 PATIENT COUNSELING INFORMATION

Advise the patient and/or caregiver to read the FDA-approved patient labeling (Patient Information).

Increases in Blood Pressure

Inform patients and/or their caregivers that mirabegron extended-release tablets may increase blood pressure. Advise patients, especially patients with hypertension, to periodically monitor their blood pressure and report increased measurement to their health care provider [see Warnings and Precautions (5.1)].

Urinary Retention

Inform patients and/or their caregivers that mirabegron extended-release tablets may cause urinary retention in adult patients with bladder outlet obstruction and in patients taking muscarinic antagonist medications for the treatment of OAB. Advise patients to contact their physician if they experience these effects while taking mirabegron extended-release tablets [see Warnings and Precautions (5.2)].

Angioedema

Inform patients and/or their caregivers that mirabegron extended-release tablets may cause angioedema. Advise patients and/or their caregivers to promptly discontinue mirabegron extended-release tablets and seek medical attention if angioedema associated with the upper airway swelling occurs as this may be life-threatening [see Warnings and Precautions (5.3)].

Drug Interactions

Advise patients to report their use of any other prescription or nonprescription medications or dietary supplements because co-administration with mirabegron extended-release tablets may require a dose adjustment and/or increased monitoring of these drugs [see Drug Interactions (7)].

Administration Instructions

Mirabegron Extended-Release Tablets:

Advise adult patients to swallow mirabegron extended-release tablets whole with water and not to chew, divide, or crush. Advise adult patients to take mirabegron extended-release tablets with or without food.

Missed Dose

Instruct patients and/or their caregivers to take any missed doses as soon as they remember, unless more than 12 hours have passed since the missed dose. If more than 12 hours have passed, the missed dose can be skipped and the next dose should be taken at the usual time.

LUPIN and the are registered trademarks of Lupin Pharmaceuticals, Inc.

Manufactured for:

Lupin Pharmaceuticals, Inc.

Naples, FL 34108

United States

Manufactured by:

Lupin Limited

Nagpur 441 108

INDIA

Revised: November 2024

Patient Information

Mirabegron (MIR-a-BEG-ron)

extended-release tablets

for oral use

What are mirabegron extended-release tablets?

- Mirabegron extended-release tablets are prescription medicine that can be used to treat adults with the following symptoms due to a condition called overactive bladder (OAB) :
  - Urge urinary incontinence: a strong need to urinate with leaking or wetting accidents
  - Urgency: a strong need to urinate right away
  - Frequency: urinating often

It is not known if mirabegron extended-release tablets are safe and effective in children under 3 years of age.

Who should not take mirabegron extended-release tablets?

Do not take mirabegron extended-release tablets if you are allergic to mirabegron or any of the ingredients in mirabegron extended-release tablets. See the end of this Patient Information leaflet for a complete list of ingredients in mirabegron extended-release tablets.

Before you take mirabegron extended-release tablets, tell your doctor about all of your medical conditions, including if you:

- have liver problems.
- have kidney problems.
- have very high uncontrolled blood pressure.
- have trouble emptying your bladder or you have a weak urine stream.
- are pregnant or plan to become pregnant. It is not known if mirabegron extended-release tablets will harm your unborn baby. Talk to your doctor if you are pregnant or plan to become pregnant.
- are breastfeeding or plan to breastfeed. It is not known if mirabegron passes into your breast milk. Talk to your doctor about the best way to feed your baby if you take mirabegron extended-release tablets.

Tell your doctor about all the medicines you take, including prescription and over-the-counter medicines, vitamins, and herbal supplements. Mirabegron extended-release tablets may affect the way other medicines work, and other medicines may affect how mirabegron extended-release tablets work.

Especially tell your doctor if you take:

- thioridazine (Mellaril or Mellaril-S)
- flecainide (Tambocor)
- propafenone (Rythmol)
- digoxin (Lanoxin)
- solifenacin succinate (VESIcare)

How should I take mirabegron extended-release tablets?

- Take mirabegron extended-release tablets exactly as your doctor tells you to take it.
- You should take 1 mirabegron extended-release tablet 1 time a day.
- You should take mirabegron extended-release tablets with water and swallow the tablet whole.
- Do not chew, break, or crush the tablet.
- Adults can take mirabegron extended-release tablets with or without food.
- If you miss a dose of mirabegron extended-release tablets, take it as soon as possible. If it has been more than 12 hours since taking the last dose of mirabegron extended-release tablets, skip that dose and take the next dose at the usual time.
- If you take too much mirabegron extended-release tablets, call your doctor or go to the nearest hospital emergency room right away.

What are the possible side effects of mirabegron extended-release tablets?

Mirabegron extended-release tablets may cause serious side effects, including:

- increased blood pressure . Mirabegron extended-release tablets may cause your blood pressure to increase or make your blood pressure worse if you have a history of high blood pressure. You and your doctor should check your blood pressure while you are taking mirabegron extended-release tablets. Call your doctor if you have increased blood pressure.
- inability to empty your bladder (urinary retention) . Mirabegron extended-release tablets may increase your chances of not being able to empty your bladder if you have bladder outlet obstruction or if you are taking other medicines to treat overactive bladder. Tell your doctor right away if you are unable to empty your bladder.
- angioedema . Mirabegron extended-release tablets may cause an allergic reaction with swelling of the lips, face, tongue, or throat with or without difficulty breathing. Stop using mirabegron extended-release tablets and go to the nearest hospital emergency room right away.

Adults with Overactive Bladder

The most common side effects of mirabegron extended-release tablets include:

- high blood pressure
- pain or swelling of the nose or throat (nasopharyngitis)
- urinary tract infection
- headache

Tell your doctor if you have any side effect that bothers you, does not go away, or if you have swelling of the face, lips, tongue or throat, hives, skin rash or itching while taking mirabegron extended-release tablets.

These are not all the possible side effects of mirabegron extended-release tablets. For more information, ask your doctor or pharmacist.

Call your doctor for medical advice about side effects.

You may report side effects to FDA at 1-800-FDA-1088 or Lupin Pharmaceuticals, Inc. at 1-800-399-2561.

How should I store mirabegron extended-release tablets?

- Store mirabegron extended-release tablets at room temperature between 68°F to 77°F (20°C to 25°C). Keep the bottle closed. Throw away (discard) medicine that is out of date or no longer needed.

Keep mirabegron extended-release tablets and all medicines out of the reach of children.

General information about the safe and effective use of mirabegron extended-release tablets.

Medicines are sometimes prescribed for purposes other than those listed in a Patient Information leaflet. Do not use mirabegron extended-release tablets for a condition for which it was not prescribed.

Do not give mirabegron extended-release tablets to other people, even if they have the same symptoms you have. It may harm them.

This leaflet summarizes the most important information about mirabegron extended-release tablets. If you would like more information, talk with your doctor. You can ask your doctor or pharmacist for information about mirabegron extended-release tablets that is written for health professionals.

What are the ingredients in mirabegron extended-release tablets?

Active ingredient: mirabegron

Inactive ingredients: butylated hydroxytoluene, D&C Yellow No.10 Aluminum Lake, FD&C Yellow No. 6, hydroxy propyl cellulose, hypromellose, magnesium stearate, microcrystalline cellulose, polyethylene glycol, polyethylene oxide, titanium dioxide, triacetin.

Pediatric use information is approved for Astellas Pharma Global Development, Inc.'s MYRBETRIQ (mirabegron extended-release tablets). However, due to Astellas Pharma Global Development, Inc.'s marketing exclusivity rights, this drug product is not labeled with that information.

The brands listed are trademarks of their respective owners and are not trademarks of Lupin Pharmaceuticals, Inc. The makers of these brands are not affiliated with and do not endorse Lupin Pharmaceuticals, Inc. or its products.

For more information, go to www.lupinpharmaceuticals.com website or call 1-800-399-2561.

This Patient Information has been approved by the U.S. Food and Drug Administration.

LUPIN and the are registered trademarks of Lupin Pharmaceuticals, Inc.

Manufactured for:

Lupin Pharmaceuticals, Inc.

Naples, FL 34108

United States

Manufactured by:

Lupin Limited

Nagpur 441 108

INDIA

Revised: November 2024 ID#:277116

PACKAGE LABEL.PRINCIPAL DISPLAY PANEL

NDC 68180-151-06

Bottle of 30 Tablets

ONCE-DAILY

Mirabegron Extended-Release Tablets, 25 mg

Rx only

NDC 68180-152-06

Bottle of 30 Tablets

ONCE-DAILY

Mirabegron Extended-Release Tablets, 50 mg

Rx only